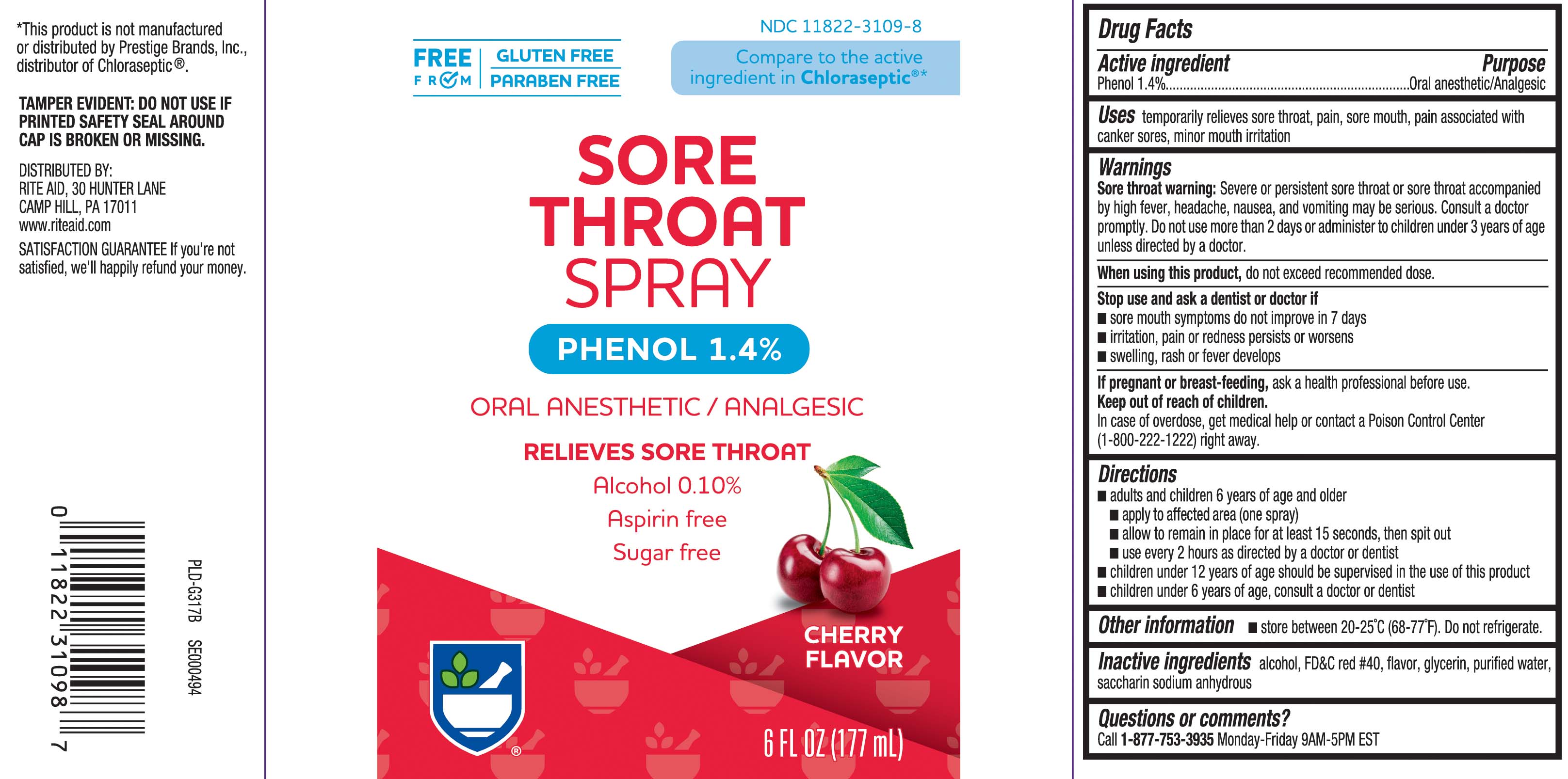 DRUG LABEL: Sore Throat
NDC: 11822-3109 | Form: SPRAY
Manufacturer: Rite Aid Corporation
Category: otc | Type: HUMAN OTC DRUG LABEL
Date: 20250711

ACTIVE INGREDIENTS: PHENOL 1.4 g/100 mL
INACTIVE INGREDIENTS: ALCOHOL; FD&C RED NO. 40; GLYCERIN; WATER; SACCHARIN SODIUM ANHYDROUS

Drug Facts

Active ingredient

Phenol 1.4%

Purpose

Oral Anesthetic/Analgesic

Uses

temporarily relieves sore throat, pain, sore mouth, pain associated with canker sores, minor mouth irritation

Warnings

Sore throat warning: Severe or persistent sore throat or sore throat accompanied by high fever, headache, nausea, and vomiting may be serious. Ask a doctor promptly. Do not use more than 2 days or administer to children under 3 years of age unless directed by a doctor.

When using this product,

do not exceed recommended dose.

Stop use and ask a dentist or doctor if

- sore mouth symptoms do not improve in 7 days
- irritation, pain or redness persists or worsens
- swelling, rash or fever develops

If pregnant or breast-feeding,

ask a health professional before use.

Keep out of reach of children.

In case of overdose, get medical help or contact a Poison Control Center (1-800-222-1222) right away.

Directions

- adults and children 6 years and older
  - apply to affected area (one spray)
  - allow to remain in place for at least 15 second, then spit out
  - use every 2 hours as directed by a doctor or dentist
- children under 12 years of age should be supervised in the use of this product
- children under 6 years of age, consult a doctor or dentist

Other information

- store between 20º-25ºC (68º-77ºF). Do not refrigerate.

Inactive ingredients

alcohol, FD&C red #40, flavor, glycerin, purified water, saccharin sodium anhydrous

Principal display panel

Compare to the active ingredient in Chloraseptic®*

SORE THROAT SPRAY

PHENOL 1.4%

ORAL ANESTHETIC/ANALGESTIC

RELIEVES SORE THROAT

Alcohol 0.10%

Aspirin free

Sugar free

CHERRY FLAVOR

FL OZ (mL)

*This product is not manufactured or distributed by Prestige Brands, Inc., distributor of Chloraseptic®.

TAMPER EVIDENT: DO NOT USE IF IPRINTED SAFETY SEAL AROUND CAP IS BROKEN OR MISSING.

DISTRIBUTED BY:

RITE AID, 30 HUNTER LANE

CAMP HILL, PA 17011

Package Label

RITE AID Sore Throat Spray Cherry Flavor